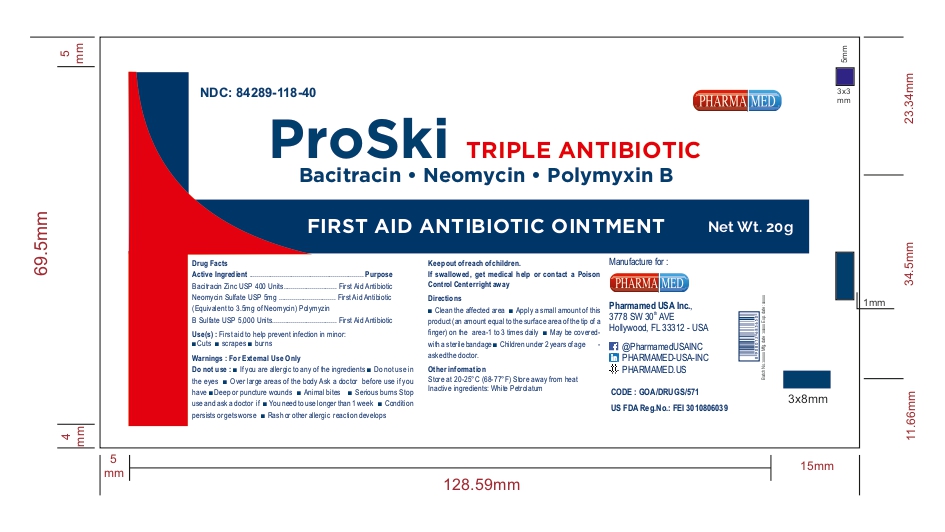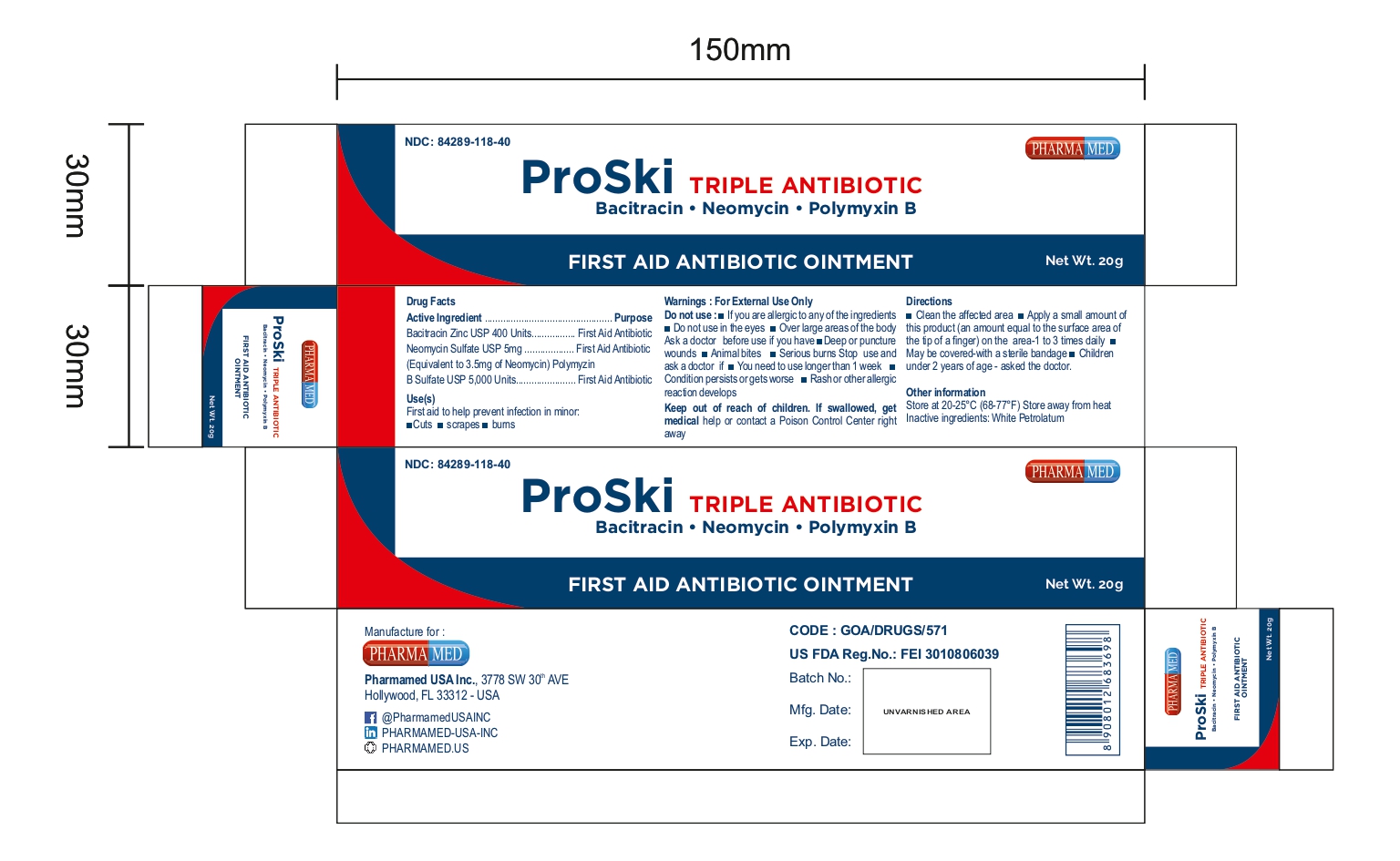 DRUG LABEL: PROSKI TRIPLE ANTIBIIOTIC
NDC: 84289-118 | Form: OINTMENT
Manufacturer: PHARMAMED USA INC
Category: otc | Type: HUMAN OTC DRUG LABEL
Date: 20250318

ACTIVE INGREDIENTS: BACITRACIN ZINC 400 [iU]/1 g; POLYMYXIN B SULFATE 5000 [iU]/1 g; NEOMYCIN SULFATE 5 mg/1 g
INACTIVE INGREDIENTS: WHITE PETROLATUM

First Aid Triple Antibiotic Ointment

ACTIVE INGREDIENT

Bacitracin Zinc (400 units per gram)

Neomycin Sulfate 5mg (equivalent to 3.5mg Neomycin per gram)

Polymyxin B Sulfate (5000 units per gram)

INDICATION

First Aid Antibiotics

USE

First aid to help prevent infection in minor cuts, scrapes, and burns

WARNING

For External Use Only.

Do not use

- In the eyes or apply over large areas of the body
- If you are allergic to any of the ingredients
- Longer than 1 week unless directed by a doctor

Ask a doctor before use if you have:

deep or puncture wounds, animal bites, or serious burns

Stop use and ask a doctor if:

The condition persists or gets worse, or if a rash or other allergic reaction develops

Keep out of reach of children:

If swallowed, get medical help or contact a Poison Control Center (1-800-222-1222) right away

DIRECTIONS

Clean the affected area. Apply a small amount of this product (an amount equal to the surface area of the tip of a finger) on the area 1 to 3 times daily. May be covered with a sterile bandage.

OTHER INFORMATION

Store at room temperature between 20º - 25ºC (68º - 77ºF)

INACTIVE INGREDIENTS

WHITE PETROLATUM

QUESTIONS OR COMMENTS?

(754)-200-8994 (Mon-Fri 8 AM to 4 PM EST)

PACKAGE / LABEL PRINCIPAL DISPLAY PANEL

NDC: 84289-118-40

FIRST AID TRIPLE ANTIBIOTIC OINTMENT
Bacitracin Neomycin Plymyxin B

Net Wt 20g

GOA/DRUGS/571